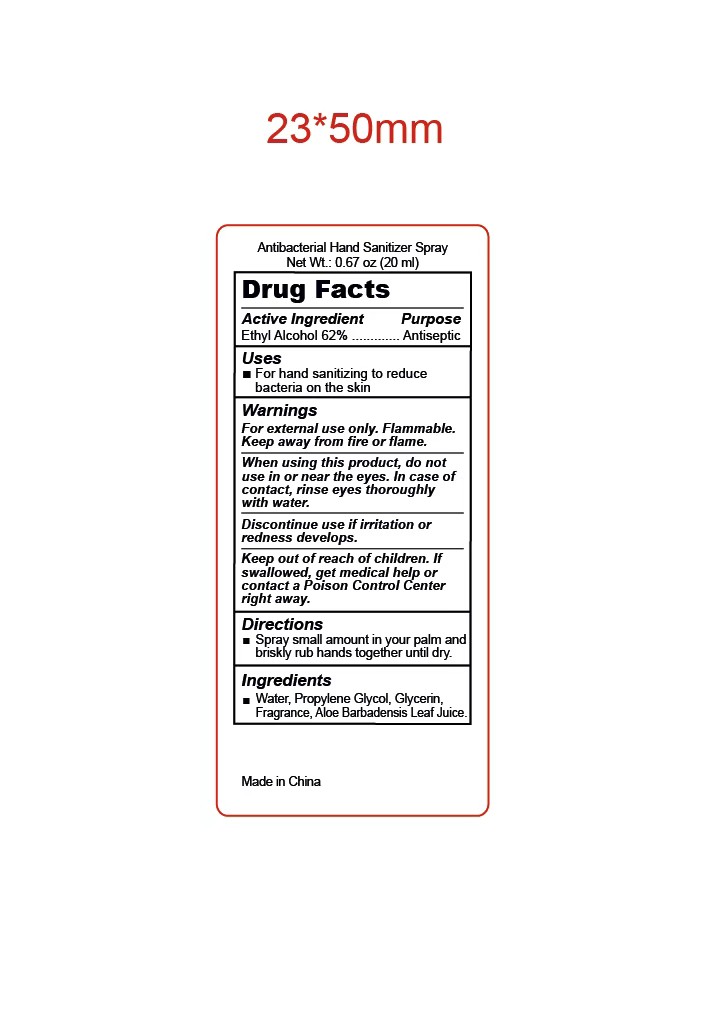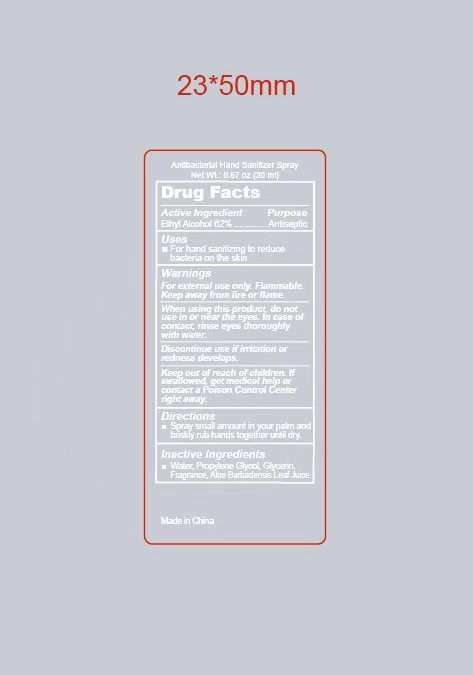 DRUG LABEL: Antibacterial Hand Sanitizer Spray.
NDC: 87001-001 | Form: LIQUID
Manufacturer: HAIAN KANGRUI TEXTILE CO., LTD.
Category: otc | Type: HUMAN OTC DRUG LABEL
Date: 20251125

ACTIVE INGREDIENTS: ALCOHOL 62 g/112 mL
INACTIVE INGREDIENTS: GLYCERIN; PROPYLENE GLYCOL; ALOE VERA LEAF; WATER

87001-001

Purpose

Antiseptic

Active Ingredient

Ethyl Alcohol 62%

Uses

For hand sanitizing to reduce bacteria on the skin.

Warnings

For external use only.

Flammable. Keep away from fire and flame.

When using this product，

do not use in or near the eyes.In case of contact，rinse eyes thoroughly with water.

Discontinue use

if irritation or redness develops.

Keep out of reach of children.

If swallowed, get medical help or contact a Poison Control Center right away.

Directions

Spray small amount in your palm and briskly rub hands together until dry.

Inactive ingredients

WATER, PROPYLENE GLYCOL, GLYCERIN, FRAGRANCE, ALOE BARBAENSIS LEAF JUICE.